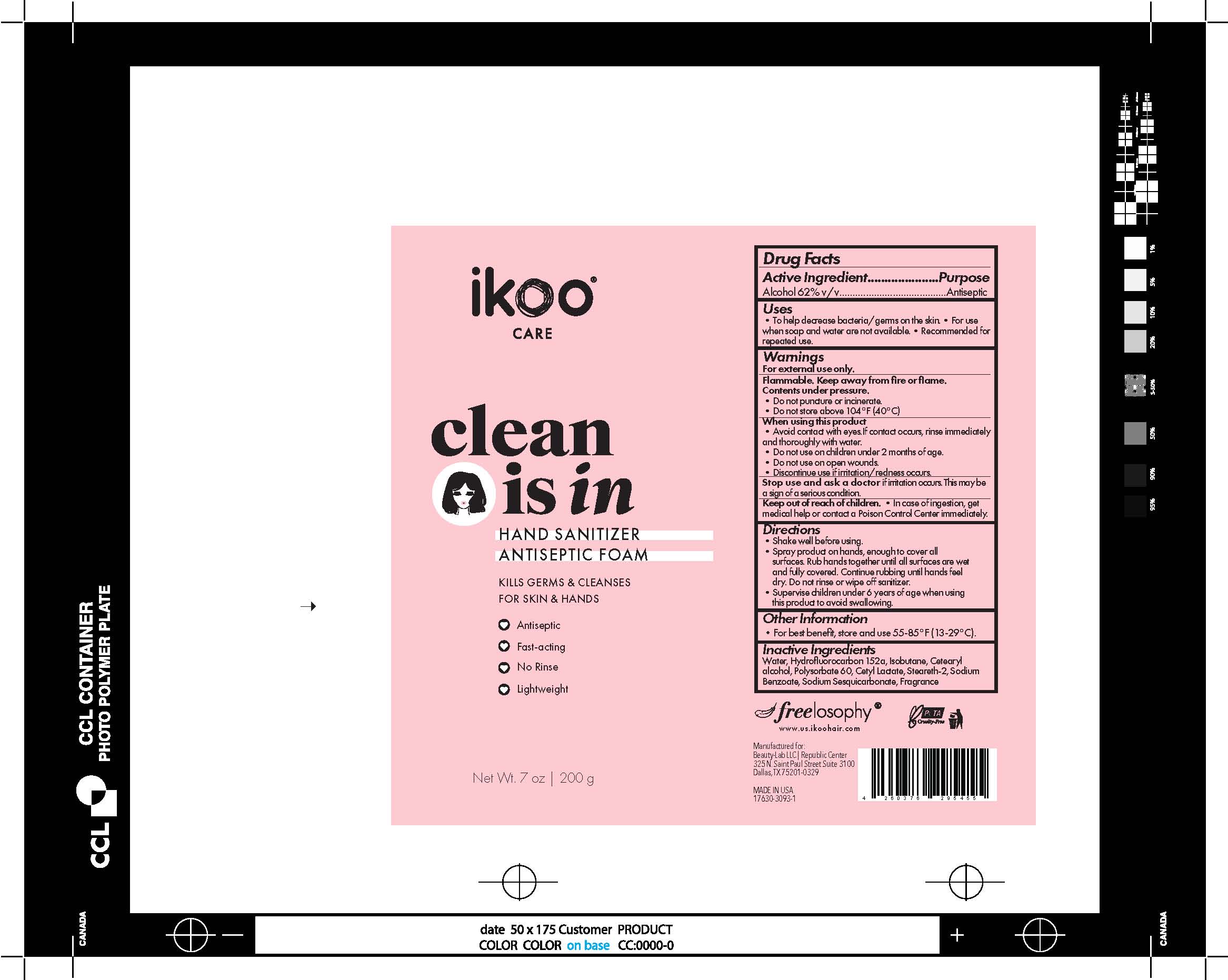 DRUG LABEL: Clean is In Hand Sanitizer Antiseptic Foam
NDC: 80473-030 | Form: AEROSOL, FOAM
Manufacturer: Beauty-Lab LLC
Category: otc | Type: HUMAN OTC DRUG LABEL
Date: 20200910

ACTIVE INGREDIENTS: ALCOHOL 62 g/100 g
INACTIVE INGREDIENTS: WATER; 1,1-DIFLUOROETHANE; Isobutane; CETOSTEARYL ALCOHOL; Polysorbate 60; Cetyl Lactate; Steareth-2; Sodium Benzoate; Sodium Sesquicarbonate

Ikoo Care clean is in Hand Sanitizer Antiseptic Foam

Warnings

For external use only.
Flammable. Keep away from fire or flame.
Contents under pressure.
•Do not puncture or incinerate.
•Do not store above 104°F (40°C)
When using this product
•Avoid contact with eyes.If contact occurs, rinse immediately
and thoroughly with water.
•Do not use on children under 2 months of age.
•Do not use on open wounds.
•Discontinue use if irritation/redness occurs.
Stop use and ask a doctor if irritation occurs. This may be
a sign of a serious condition.
Keep out of reach of children. •In case of ingestion, get
medical help or contact a Poison Control Center immediately.

Inactive Ingredients

Water, Hydrofluorocarbon 152a, Isobutane, Cetearyl
alcohol, Polysorbate 60, Cetyl Lactate, Steareth-2, Sodium
Benzoate, Sodium Sesquicarbonate, Fragrance

Active Ingredients

Active Ingredient.....................Purpose
Alcohol 62% v/v........................................Antiseptic

Purpose

Active Ingredient.....................Purpose
Alcohol 62% v/v........................................Antiseptic

Keep out of reach of children. •In case of ingestion, get
medical help or contact a Poison Control Center immediately.

Uses

•To help decrease bacteria/germs on the skin.•For use
when soap and water are not available.•Recommended for
repeated use.

Dosage

•Spray product on hands, enough to cover all
surfaces. Rub hands together until all surfaces are wet
and fully covered. Continue rubbing until hands feel
dry. Do not rinse or wipe off sanitizer.

Warnings

For external use only.
Flammable. Keep away from fire or flame.
Contents under pressure.
•Do not puncture or incinerate.
•Do not store above 104°F (40°C)
When using this product
•Avoid contact with eyes.If contact occurs, rinse immediately
and thoroughly with water.
•Do not use on children under 2 months of age.
•Do not use on open wounds.
•Discontinue use if irritation/redness occurs.
Stop use and ask a doctor if irritation occurs. This may be
a sign of a serious condition.
Keep out of reach of children. •In case of ingestion, get
medical help or contact a Poison Control Center immediately.